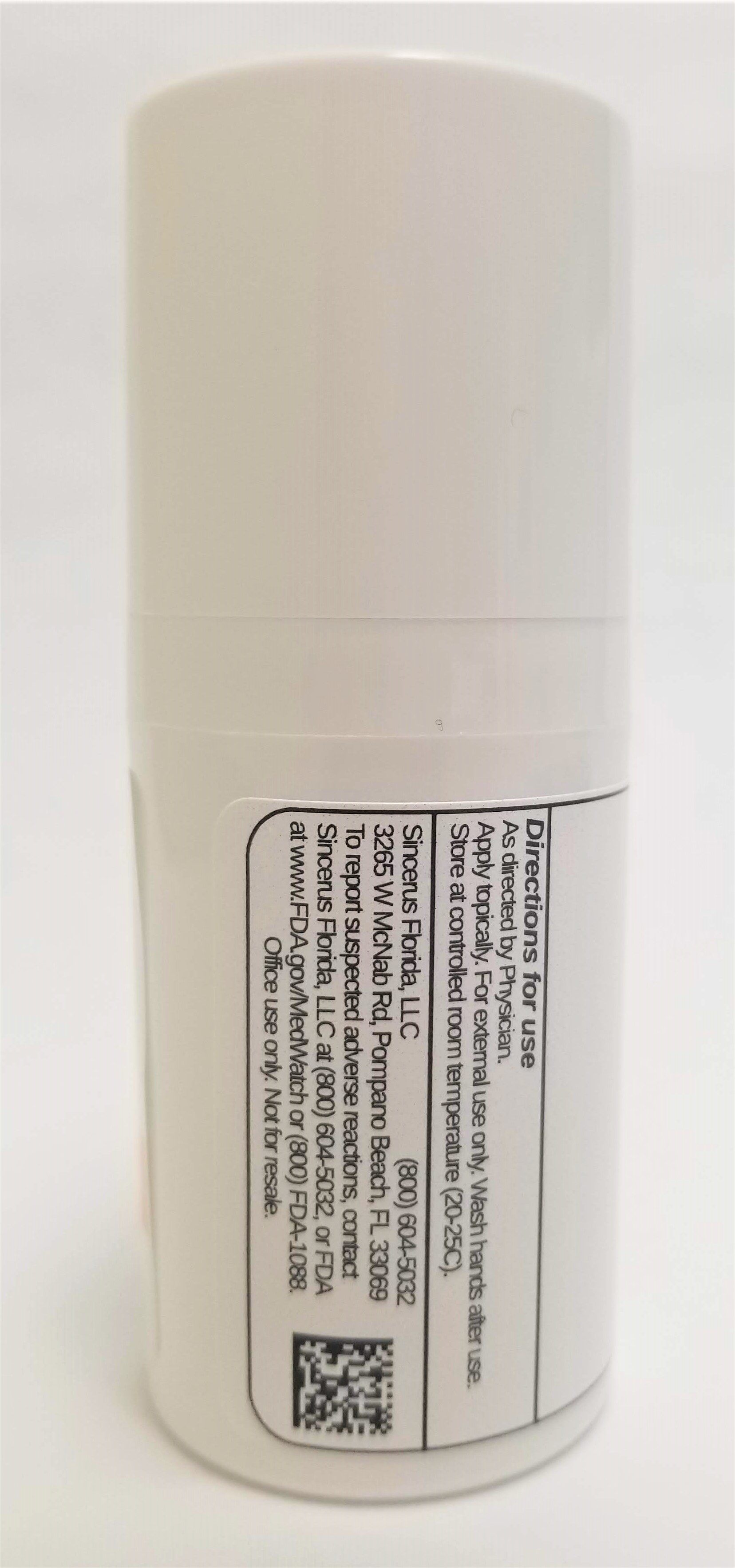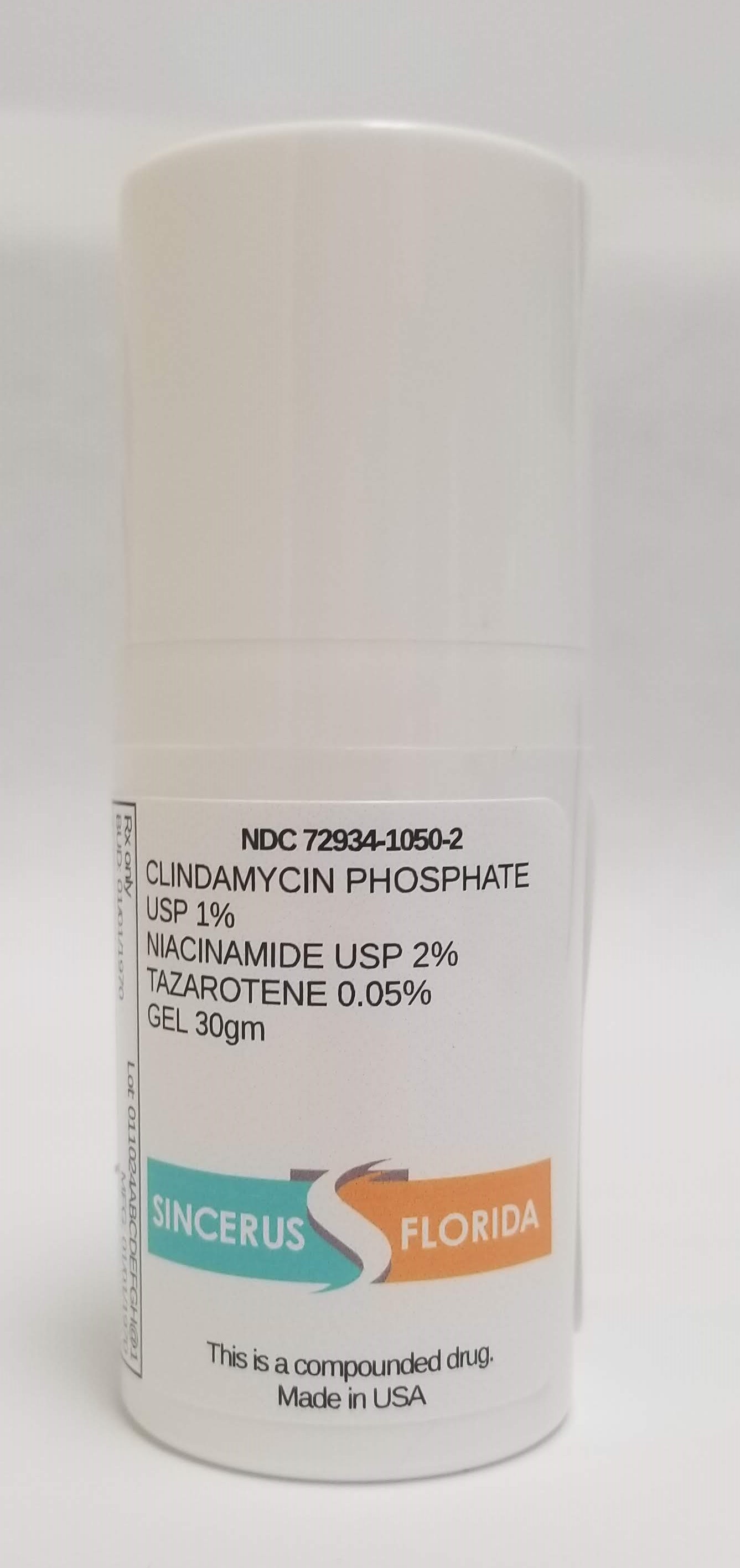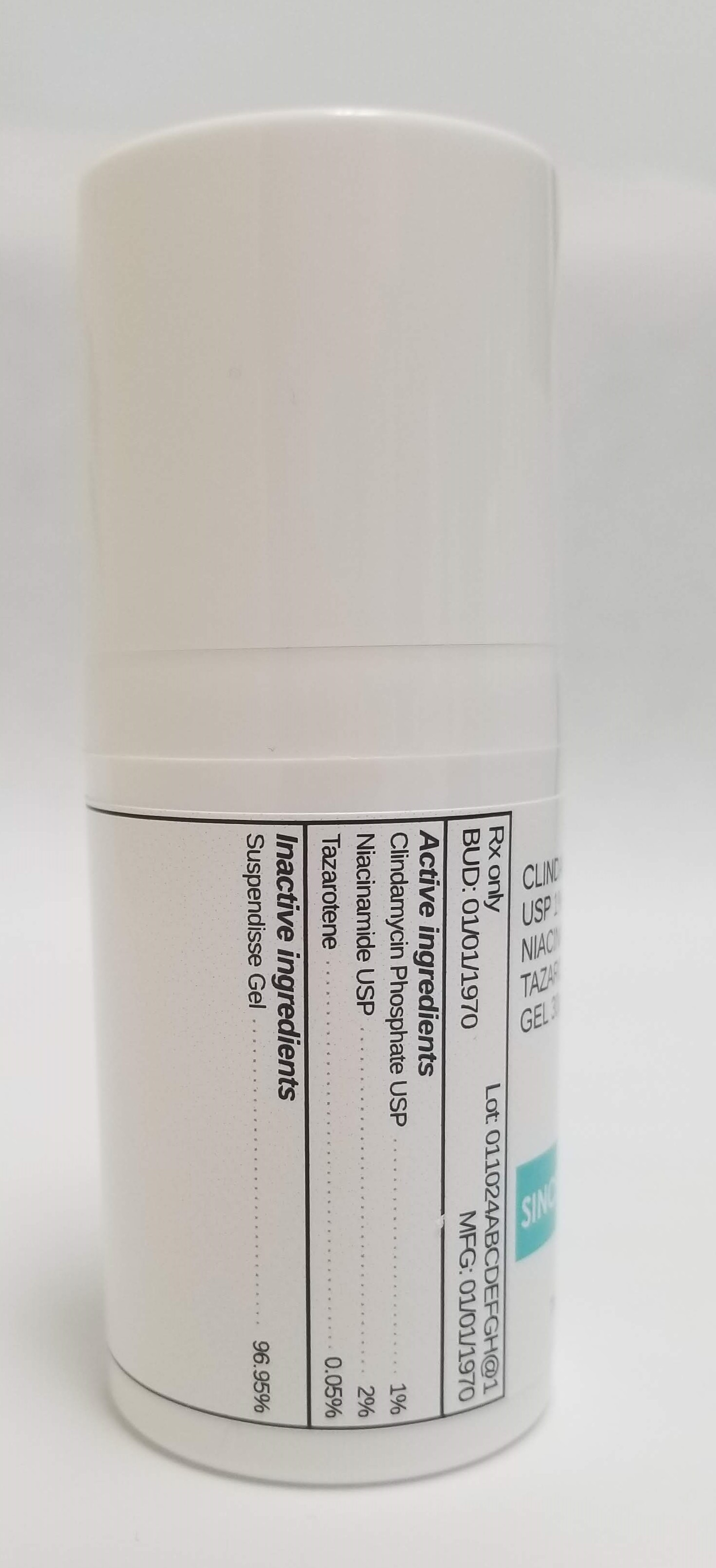 DRUG LABEL: CLINDAMYCIN 1% / NIACINAMIDE 2% / TAZAROTENE 0.05%
NDC: 72934-1050 | Form: GEL
Manufacturer: Sincerus Florida, LLC
Category: prescription | Type: HUMAN PRESCRIPTION DRUG LABEL
Date: 20190509

ACTIVE INGREDIENTS: TAZAROTENE 0.05 g/100 g; NIACINAMIDE 2 g/100 g; CLINDAMYCIN PHOSPHATE 1 g/100 g

CLINDAMYCIN 1% / NIACINAMIDE 2% / TAZAROTENE 0.05%